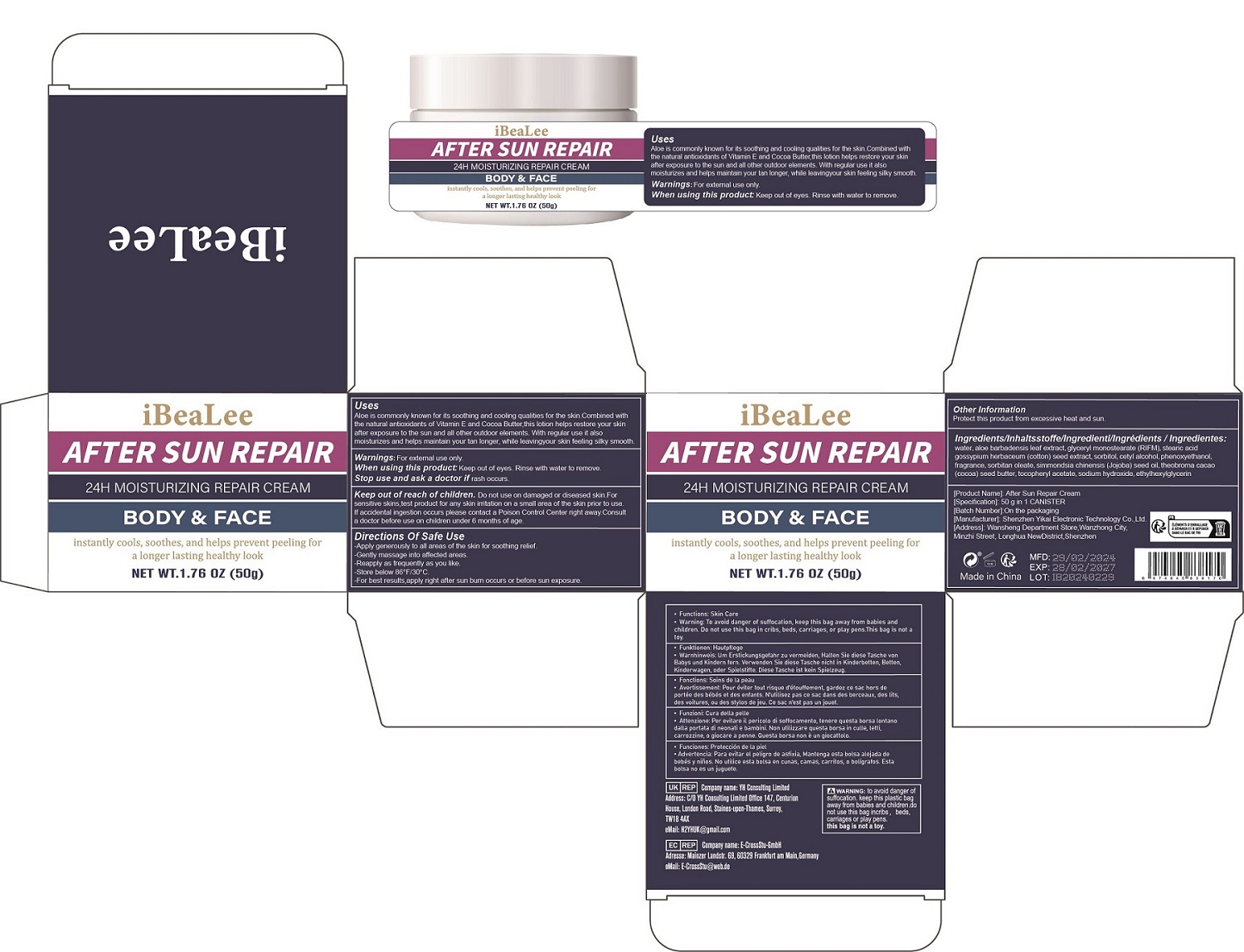 DRUG LABEL: After Sun Repair Cream
NDC: 84117-003 | Form: CREAM
Manufacturer: Shenzhen Hengkaifeng Commerce and Trade Co., Ltd
Category: otc | Type: HUMAN OTC DRUG LABEL
Date: 20240328

ACTIVE INGREDIENTS: ALOE VERA LEAF 33 g/100 g
INACTIVE INGREDIENTS: WATER; GLYCERYL MONOSTEARATE; STEARIC ACID; LEVANT COTTON SEED; SORBITOL; CETYL ALCOHOL; PHENOXYETHANOL; FRAGRANCE 13576; SORBITAN MONOOLEATE; JOJOBA OIL; COCOA BUTTER; .ALPHA.-TOCOPHEROL ACETATE; ETHYLHEXYLGLYCERIN; SODIUM HYDROXIDE

ACTIVE INGREDIENT

aloe barbadensis leaf extract 33%

Purpose

AFTER SUN REPAIR

Use

Aloe is commonly known for its soothing and cooling qualities for the skin.Combined with
the natural antioxidants of Vitamin E and Cocoa Butter,this lotion helps restore your skin
after exposure to the sun and all other outdoor elements. With regular use it also
moisturizes and helps maintain your tan longer, while leavingyour skin feeling silky smooth.

Warnings

For external use only

Do not use

on damaged or broken skin

When Using

Keep out of eyes. Rinse with water to remove.

Stop Use

rash occurs

Keep Oot Of Reach Of Children

Do not use on damaged or diseased skin.For
sensitive skins,test product for any skin irritation on a small area of the skin prior to use.
If accidental ingestion occurs please contact a Poison Control Center right away.Consult
a doctor before use on children under 6 months of age.

Directions

-Apply generously to all areas of the skin for soothing relief.
-Gently massage into affected areas.
-Reapply as frequently as you like.
-Store below 86°F/30°C.
-For best results,apply right after sun burn occurs or before sun exposure.

Inactive ingredients

water,glyceryl monostearate (RIFM), stearic acid
gossypium herbaceum (cotton) seed extract, sorbitol, cetyl alcohol, phenoxyethanol,
fragrance, sorbitan oleate, simmondsia chinensis (Jojoba) seed oil, theobroma cacao
(cocoa) seed butter, tocopheryl acetate, sodium hydroxide, ethylhexylglycerin

Other information

Protect this product from excessive heat and sun.